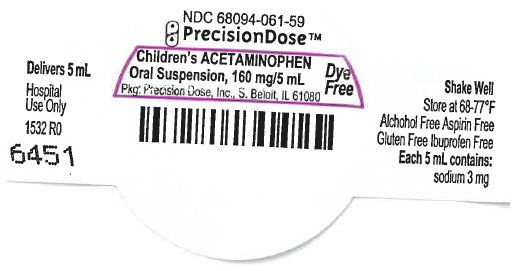 DRUG LABEL: Dye Free Childrens Acetaminophen
NDC: 68094-061 | Form: SUSPENSION
Manufacturer: Precision Dose Inc.
Category: otc | Type: HUMAN OTC DRUG LABEL
Date: 20250116

ACTIVE INGREDIENTS: Acetaminophen 160 mg/5 mL
INACTIVE INGREDIENTS: ANHYDROUS CITRIC ACID; CALCIUM SULFATE, UNSPECIFIED FORM; CARRAGEENAN; GLYCERIN; MICROCRYSTALLINE CELLULOSE; CARBOXYMETHYLCELLULOSE SODIUM, UNSPECIFIED; PROPYLENE GLYCOL; PROPYLPARABEN; WATER; SODIUM BENZOATE; SORBITOL; SUCRALOSE; SODIUM PHOSPHATE, TRIBASIC

DYE FREE CHILDREN'S ACETAMINOPHEN
ORAL SUSPENSION

Drug Facts

Active ingredient (in each 5 mL)

Acetaminophen 160 mg

Purpose

Pain reliever/fever reducer

Uses

temporarily:

- reduces fever
- relieves minor aches and pains due to:
  - the common cold
  - flu
  - headache
  - sore throat
  - toothache

Warnings

Liver warning

This product contains acetaminophen. Severe liver damage may occur if your child takes

- more than 5 doses in 24 hours, which is the maximum daily amount
- with other drugs containing acetaminophen

Allergy alert

Acetaminophen may cause a severe skin reactions. Symptoms may include:

- skin reddening
- blisters
- rash

If a skin reaction occurs, stop use and seek medical help right away.

Sore throat warning

If sore throat is severe, persists for more than 2 days, is accompanied or followed by fever, headache, rash, nausea, or vomiting, consult a doctor promptly.

Do not use

- with any other drug containing acetaminophen (prescription or nonprescription). If you are not sure whether a drug contains acetaminophen, ask a doctor or pharmacist.
- if your child has ever had an allergic reaction to this product or any of its ingredients

Ask a doctor before use if your child has liver disease

Ask a doctor or pharmacist before use if your child is taking the blood thinning drug warfarin

When using this product do not exceed recommended dose (see overdose warning)

Stop use and ask a doctor if

- pain gets worse or lasts more than 5 days
- fever gets worse or lasts more than 3 days
- new symptoms occur
- redness or swelling is present

These could be signs of a serious condition.

Keep out of reach of children.

Overdose warning

In case of overdose, get medical help or contact a Poison Control Center right away (1-800-222-1222). Quick medical attention is critical even if you do not notice any signs or symptoms.

Directions

- Use as directed per healthcare professional.
- this product does not contain directions or complete warnings for adult use
- do not give more than directed (see overdose warning)
- shake well before using
- mL = milliliter
- find right dose on chart below. If possible, use weight to dose; otherwise, use age.
- repeat dose every 4 hours while symptoms last
- do not give more than 5 times in 24 hours

Weight (lb) | Age (yr) | Dose (mL) [or as directed by a doctor]
under 24 | under 2 years | ask a doctor
24-35 | 2-3 years | 5 mL
36-47 | 4-5 years | 7.5 mL
48-59 | 6-8 years | 10 mL
60-71 | 9-10 years | 12.5 mL
72-95 | 11 years | 15 mL

Other information

- each 5 mL contains: sodium 3 mg
- store at 20-25°C (68-77°F)

Inactive ingredients

anhydrous citric acid, calcium sulfate, carrageenan, flavor, glycerin, hydroxyethyl cellulose, microcrystalline cellulose and carboxymethylcellulose sodium, propylene glycol, purified water, sodium benzoate, sorbitol solution, sucralose, tribasic sodium phosphate

Alcohol Free, Aspirin Free, Dye Free, Gluten Free, Ibuprofen Free

Questions or comments?

1-800-397-9228

How Supplied

NDC 68094-061-61
5 mL per unit dose cup
One hundred (100) cups per shipper

NDC 68094-061-62
5 mL per unit dose cup
Thirty (30) cups per shipper

Distributed By
Perrigo Company
Allegan, MI 49010

Packaged By
Precision Dose, Inc.
South Beloit, IL 61080

QUESTIONS

For inquiries call Precision Dose, Inc. at 1-800-397-9228 or email druginfo@precisiondose.com

LI1531 Rev. 02/23

PRINCIPAL DISPLAY PANEL - 5 mL Cup Label

NDC 68094-061-59

PrecisionDose™

Children's ACETAMINOPHEN
Oral Suspension, 160 mg/5 mL

Dye
Free

Pkg: Precision Dose, Inc., S. Beloit, IL 61080